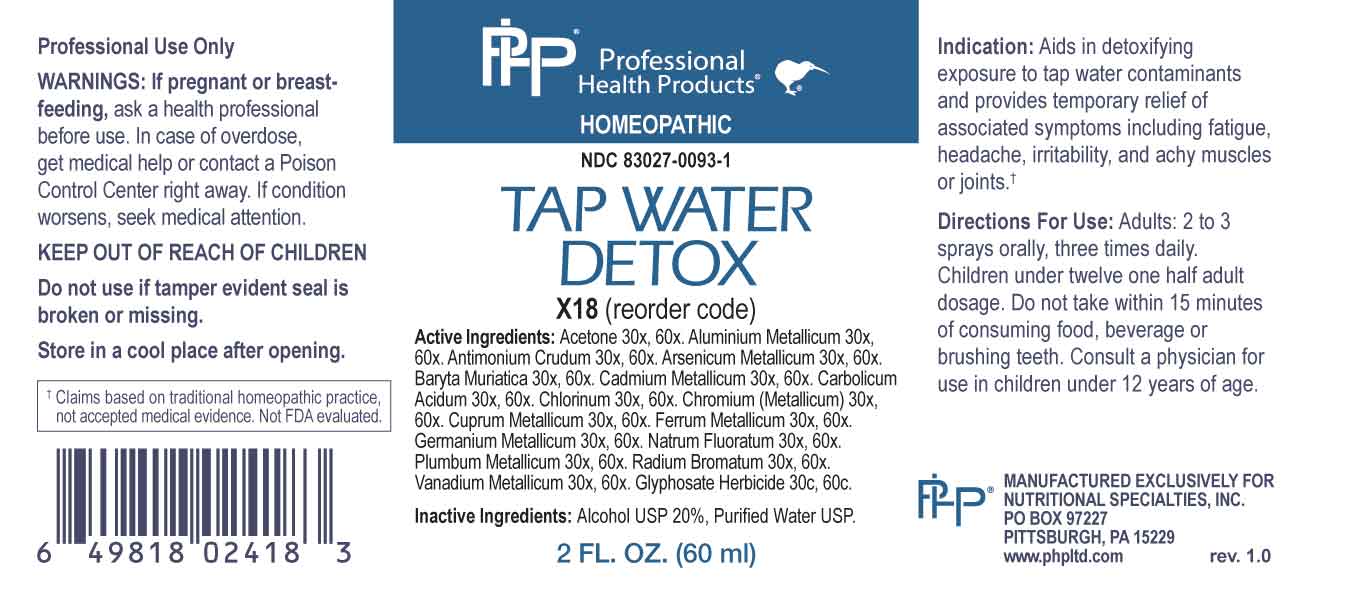 DRUG LABEL: Tap Water Detox
NDC: 83027-0093 | Form: SPRAY
Manufacturer: Nutritional Specialties, Inc.
Category: homeopathic | Type: HUMAN OTC DRUG LABEL
Date: 20230711

ACTIVE INGREDIENTS: ACETONE 30 [hp_X]/1 mL; ALUMINUM 30 [hp_X]/1 mL; ANTIMONY TRISULFIDE 30 [hp_X]/1 mL; ARSENIC 30 [hp_X]/1 mL; BARIUM CHLORIDE DIHYDRATE 30 [hp_X]/1 mL; CADMIUM 30 [hp_X]/1 mL; PHENOL 30 [hp_X]/1 mL; CHLORINE 30 [hp_X]/1 mL; CHROMIUM 30 [hp_X]/1 mL; COPPER 30 [hp_X]/1 mL; IRON 30 [hp_X]/1 mL; GERMANIUM 30 [hp_X]/1 mL; SODIUM FLUORIDE 30 [hp_X]/1 mL; LEAD 30 [hp_X]/1 mL; RADIUM BROMIDE 30 [hp_X]/1 mL; VANADIUM 30 [hp_X]/1 mL; GLYPHOSATE 30 [hp_C]/1 mL
INACTIVE INGREDIENTS: WATER; ALCOHOL

DRUG FACTS:

ACTIVE INGREDIENTS:

Acetone 30X, 60X, Aluminium Metallicum 30X, 60X, Antimonium Crudum 30, 60X, Arsenicum Metallicum 30X, 60X, Baryta Muriatica 30X, 60X, Cadmium Metallicum 30X, 60X, Carbolicum Acidum 30X, 60X, Chlorinum 30X, 60X, Chromium (Metallicum) 30X, 60X, Cuprum Metallicum 30X, 60X, Ferrum Metallicum 30X, 60X, Germanium Metallicum 30X, 60X, Natrum Fluoratum 30X, 60X, Plumbum Metallicum 30X, 60X, Radium Bromatum 30X, 60X, Vanadium Metallicum 30X, 60X, Glyphosate Herbicide 30C, 60C.

PURPOSE:

Aids in detoxifying exposure to tap water contaminants and provides temporary relief of associated symptoms including fatigue, headache, irritability, and achy muscles or joints†

†Claims based on traditional homeopathic practice, not accepted medical evidence. Not FDA evaluated.

WARNINGS:

Professional Use Only

If pregnant or breast-feeding, ask a health professional before use.

In case of overdose, get medical help or contact a Poison Control Center right away.

If condition worsens, seek medical attention.

KEEP OUT OF REACH OF CHILDREN

Do not use if tamper evident seal is broken or missing.

Store in a cool place after opening

KEEP OUT OF REACH OF CHILDREN:

In case of overdose, get medical help or contact a Poison Control Center right away.

DIRECTIONS:

Adults: 2 to 3 sprays orally, three times daily. Children under twelve one half adult dosage. Do not take within 15 minutes of consuming food, beverage or brushing teeth. Consult a physician for use in children under 12 years of age.

INDICATIONS

Aids in detoxifying exposure to tap water contaminants and provides temporary relief of associated symptoms including fatigue, headache, irritability, and achy muscles or joints†

†Claims based on traditional homeopathic practice, not accepted medical evidence. Not FDA evaluated.

INACTIVE INGREDIENTS:

Alcohol USP 20%, Purified Water USP.

QUESTIONS:

MANUFACTURED EXCLUSIVELY FOR

NUTRITIONAL SPECIALTIES, INC.

PO BOX 97227

PITTSBURG, PA 15229

www.phpltd.com

PACKAGE LABEL DISPLAY:

Professional

Health Products

HOMEOPATHIC

NDC 83027-0093-1

TAP WATER

DETOX

2 FL. OZ (60 ml)